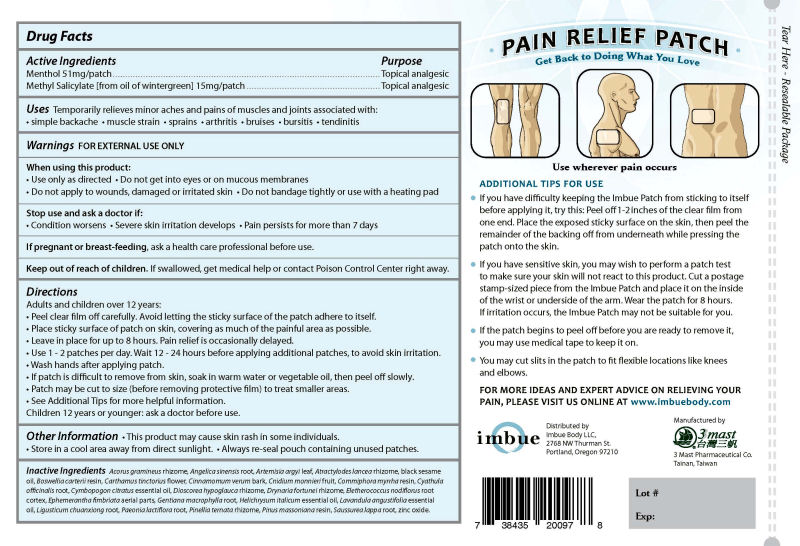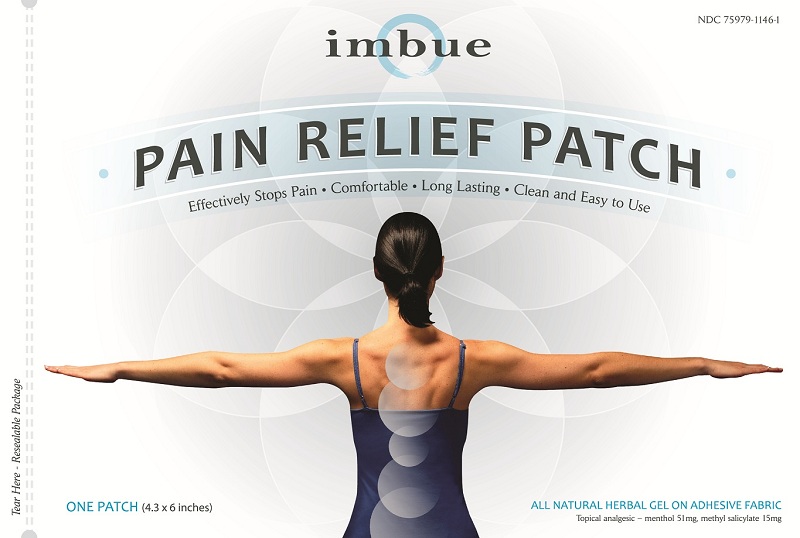 DRUG LABEL: Imbue
NDC: 75979-1146 | Form: PATCH
Manufacturer: Imbue Body LLC
Category: otc | Type: HUMAN OTC DRUG LABEL
Date: 20110201

ACTIVE INGREDIENTS: Menthol 51 mg/1 1; Methyl salicylate 15 mg/1 1
INACTIVE INGREDIENTS: Acorus gramineus root; Angelica sinensis root; Artemisia argyi leaf; Atractylodes lancea root; Sesame oil; Frankincense; Safflower; Cinnamon; Cnidium monnieri fruit; Myrrh; Cyathula officinalis root; West Indian lemongrass oil; HELICHRYSUM ITALICUM FLOWER OIL; LAVENDER OIL; LIGUSTICUM SINENSE SUBSP. CHUANXIONG ROOT; PAEONIA LACTIFLORA ROOT; SAUSSUREA COSTUS ROOT; Zinc oxide; Dioscorea collettii var. hypoglauca root; Drynaria fortunei root; Flickingeria fimbriata stem; Gentiana macrophylla root; PINELLIA TERNATA ROOT; Pinus massoniana resin; Rosin

Drug Facts

Active Ingredients

Menthol 51 mg / patch

Methyl Salicylate 15 mg / patch

Purpose

Topical Analgesic

Topical Analgesic

INDICATIONS AND USAGE

Uses: Temporarily relieves minor aches and pains of muscles and joints associated with:

• simple backache • muscle strain • sprains • arthritis • bruises • bursitis • tendinitis.

Warnings FOR EXTERNAL USE ONLY

When using this product:

• Use only as directed

• Do not get into eyes or on mucus membranes

• Do not apply to wounds, damaged or irritated skin

• Do not bandage tightly or use with a heating pad

Stop use and ask a doctor if:

• Condition worsens

• Severe skin irritation develops

• Pain persists for more than 7 days

PREGNANCY OR BREAST FEEDING

If pregnant or breastfeeding, ask a health care professional before use.

Keep out of reach of children. If swallowed, get medical help or contact a Poison Control Center right away.

Directions

Adults and children over 12 years:

• Peel clear film off carefully. Avoid letting the sticky surface of the patch adhere to itself.

• Place sticky surface of patch on skin, covering as much of the painful area as possible.

• Leave in place for up to 8 hours. Pain relief is occasionally delayed.

• Use 1 - 2 patches per day. Wait 12 - 24 hours before applying additional patches, to avoid skin irritation.

• Wash hands after applying patch.

• If patch is difficult to remove from skin, soak in warm water or vegetable oil, then peel off slowly.

• Patch may be cut to size (before removing protective film) to treat smaller areas.

• See Additional Tips for more helpful information.

Children 12 years or younger: ask a doctor before use.

Other Information

• This product may cause skin rash in some individuals.

• Store in a cool area away from direct sunlight.

• Always re-seal pouch containing unused patches.

INACTIVE INGREDIENT

Inactive Ingredients: Acorus gramineus rhizome, Angelica sinensis root, Artemisia argyi leaf, Atractylodes lancea rhizome, black sesame oil, Boswellia carterii resin, Carthamus tinctorius flower, Cinnamomum verum bark, Cnidium monnieri fruit, Commiphora myrrha resin, Cyathula officinalis root, Cymbopogon citratus essential oil, Dioscorea hypoglauca rhizome, Drynaria fortunei rhizome, Eletherococcus nodiflorus root cortex, Ephemerantha fimbriata aerial parts, Gentiana macrophylla root, Helichrysum italicum essential oil, Lavandula angustifolia essential oil, Ligusticum chuanxiong root, Paeonia lactiflora root, Pinellia ternata rhizome, Pinus massoniana resin, Saussurea lappa root, zinc oxide.